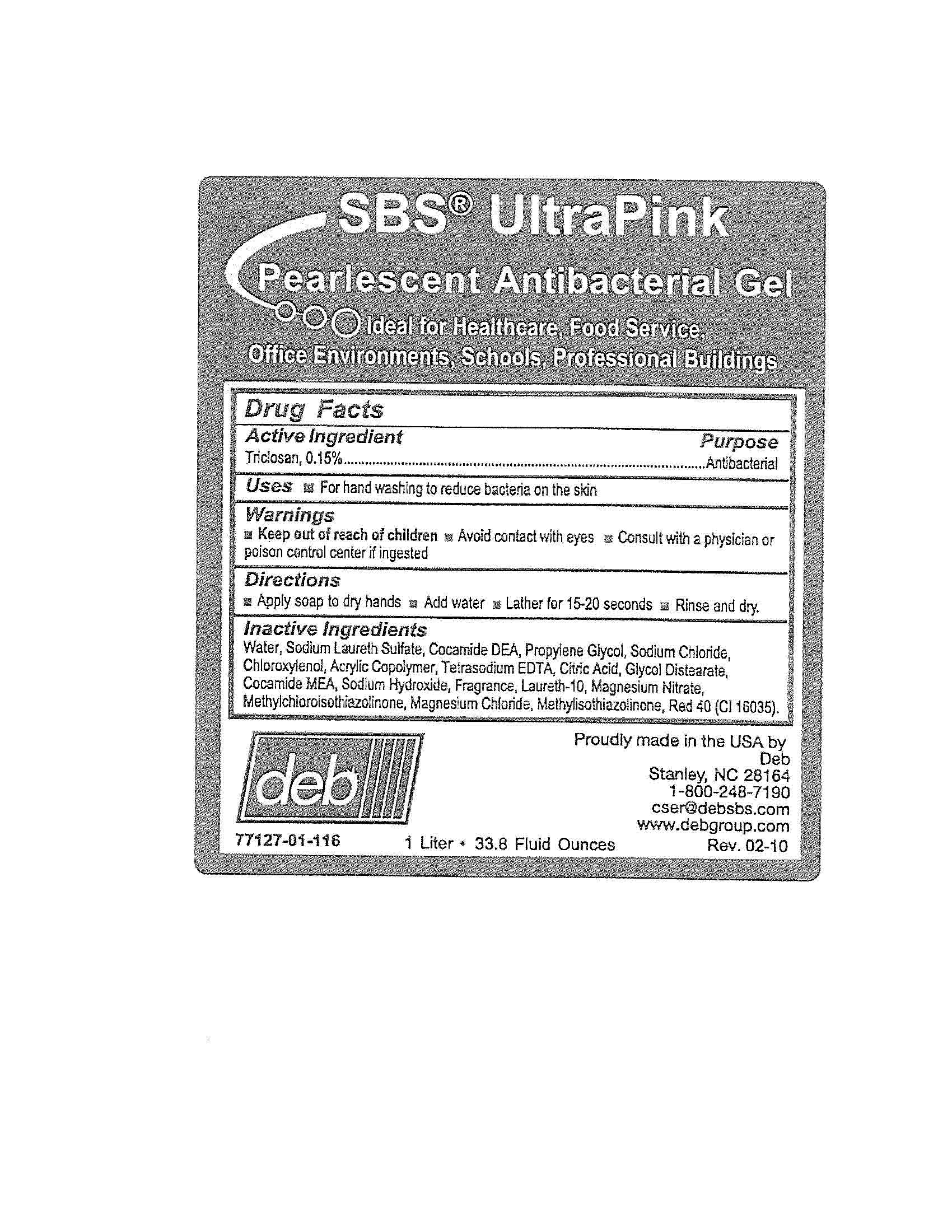 DRUG LABEL: SBS UltraPink
NDC: 11084-077 | Form: GEL
Manufacturer: Deb USA, Inc.
Category: otc | Type: HUMAN OTC DRUG LABEL
Date: 20100909

ACTIVE INGREDIENTS: TRICLOSAN 0.15 mL/100 mL
INACTIVE INGREDIENTS: WATER; SODIUM LAURETH SULFATE; COCO DIETHANOLAMIDE; PROPYLENE GLYCOL; SODIUM CHLORIDE; CHLOROXYLENOL; EDETATE SODIUM; ANHYDROUS CITRIC ACID; SODIUM HYDROXIDE; FD&C RED NO. 40; METHYLCHLOROISOTHIAZOLINONE; METHYLISOTHIAZOLINONE; MAGNESIUM NITRATE; MAGNESIUM CHLORIDE

Drug Facts

Active Ingredient

Triclosan, 0.15%

Purpose

Antibacterial

Uses

For handwashing to reduce bacteria on the skin

Warnings

Avoid contact with eyes

Keep out of reach of children

Consult with a physician or poison control center if ingested

Directions

Apply soap to dry hands

Add water

Lather for 15-20 seconds

Rinse and dry

Inactive Ingredients

Water, Sodium Laureth Sulfate, Cocamide DEA, Propylene Glycol, Sodium Chloride, Chloroxylenol, Acrylic Copolymer, Tetrasodium EDTA, Citric Acid, Glycol Distearate, Cocamide MEA, Sodium Hydroxide, Fragrance, Laureth-10, Magnesium Nitrate, Methylchloroisothiazolinone, Magnesium Chloride, Methylisothiazolinone, Red 40 (CI16035).

PACKAGE LABEL

SBS UltaPink

Pearlescent Antibacterial Gel

Ideal for Healthcare, Food Services, Office Environments, Schools, Professional Buildings

Proudly made in the USA

77127-01-116

1 Liter - 33.8 Fluid Ounces